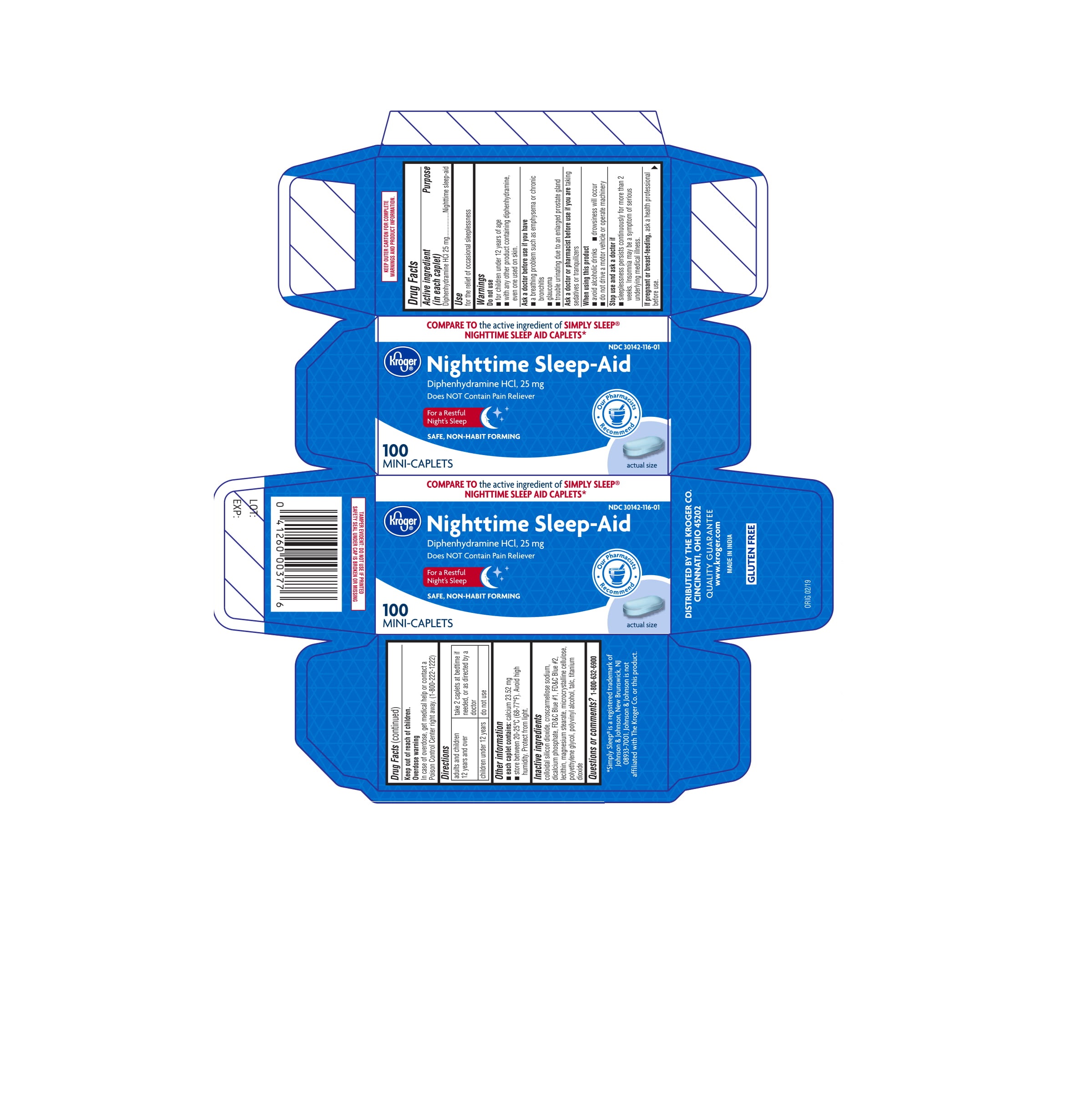 DRUG LABEL: Kroger NIGHTTIME SLEEP AID
NDC: 30142-116 | Form: TABLET
Manufacturer: KROGER COMPANY
Category: otc | Type: HUMAN OTC DRUG LABEL
Date: 20221123

ACTIVE INGREDIENTS: DIPHENHYDRAMINE HYDROCHLORIDE 25 mg/1 1
INACTIVE INGREDIENTS: SILICON DIOXIDE; CROSCARMELLOSE SODIUM; ANHYDROUS DIBASIC CALCIUM PHOSPHATE; FD&C BLUE NO. 1; FD&C BLUE NO. 2; LECITHIN, SOYBEAN; MAGNESIUM STEARATE; MICROCRYSTALLINE CELLULOSE; POLYETHYLENE GLYCOL, UNSPECIFIED; POLYVINYL ALCOHOL, UNSPECIFIED; TALC; TITANIUM DIOXIDE

Kroger NIGHTTIME SLEEP AID

Active ingredient (in each caplet)

Diphenhydramine HCl 25 mg

Purpose

Nighttime sleep-aid

Use

for the relief of occasional sleeplessness

Warnings

Do not use

■ for children under 12 years of age
■ with any other product containing diphenhydramine,
even one used on skin.

Ask a doctor before use if you have

■ a breathing problem such as emphysema or chronic
bronchitis
■ glaucoma
■ trouble urinating due to an enlarged prostate gland

Ask a doctor or pharmacist before use if you are taking
sedatives or tranquilizers

When using this product

■ avoid alcoholic drinks ■ drowsiness will occur
■ do not drive a motor vehicle or operate machinery

Stop use and ask a doctor if

sleeplessness persists continuously for more than 2
weeks. Insomnia may be a symptom of serious
underlying medical illness.

PREGNANCY OR BREAST FEEDING

If pregnant or breast-feeding, ask a health professional
before use.

Drug Facts (continued)

Keep out of reach of children.

Overdose warning

In case of overdose, get medical help or contact a
Poison Control Center right away. (1-800-222-1222)

Directions

adults and children 12 years and over | take 2 caplets at bedtime if needed, or as directed by a doctor
children under 12 years | do not use

Other information

■ each caplet contains: calcium 23.52 mg
■ store between 20-25°C (68-77°F). Avoid high
humidity. Protect from light.

Inactive ingredients

colloidal silicon dioxide, croscarmellose sodium,
dicalcium phosphate, FD&C Blue #1, FD&C Blue #2,
lecithin, magnesium stearate, microcrystalline cellulose,
polyethylene glycol, polyvinyl alcohol, talc, titanium
dioxide

Questions or comments? 1-800-632-6900

PRINCIPAL DISPLAY PANEL

COMPARE TO the active ingredient of SIMPLY SLEEP ® NIGHTTIME SLEEP AID CAPLETS*

Kroger

NDC 30142-116-01

Nighttime Sleep-Aid

Diphenhydramine HCl, 25mg

Does NOT contain Pain Reliever

For a Restful

Night's Sleep

SAFE, NON-HABIT FORMING

100

MINI-CAPLETS

actual size

*Simply Sleep® is a registered trademark of Johnson & Johnson, New Brunswick, NJ 08933-7001. Johnson & Johnson is not affiliated with The Kroger Co. or this product.